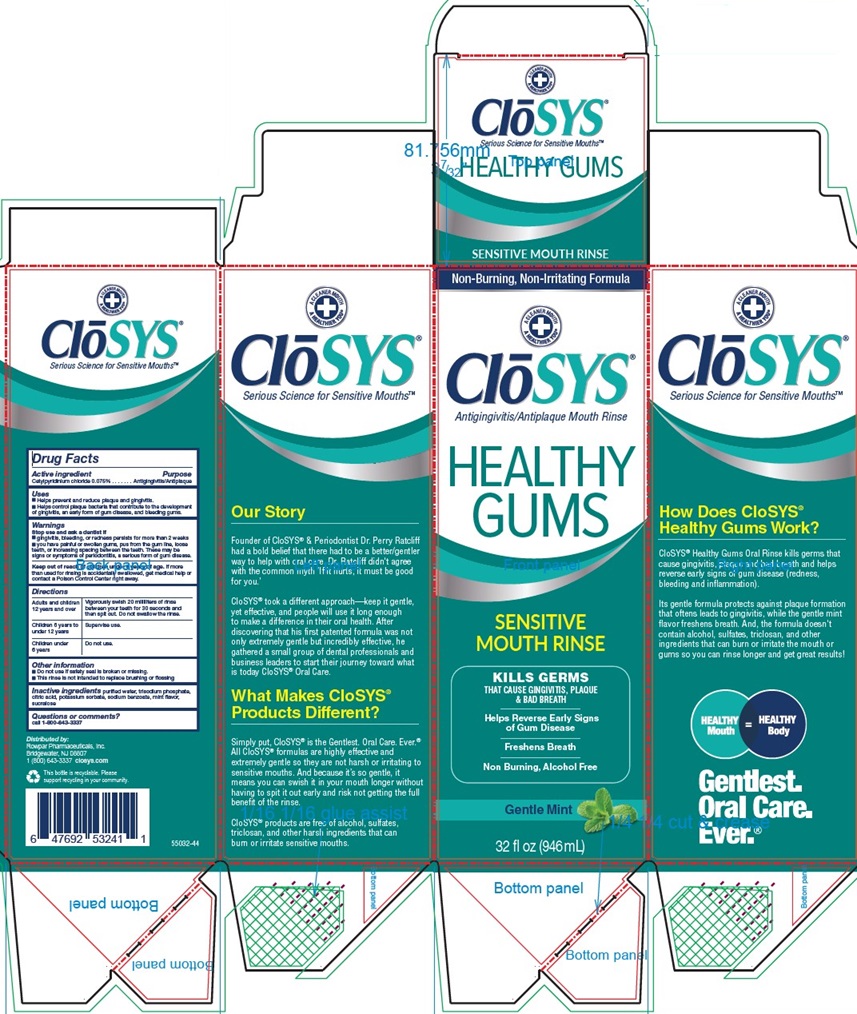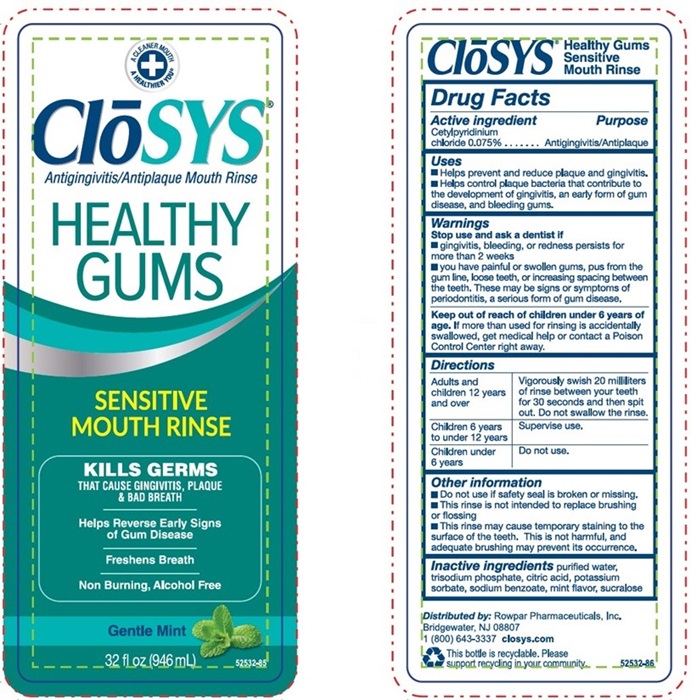 DRUG LABEL: CloSYS Silver Healthy Gums
NDC: 58578-0407 | Form: LIQUID
Manufacturer: Rowpar Pharmaceuticals, Inc.
Category: otc | Type: HUMAN OTC DRUG LABEL
Date: 20250516

ACTIVE INGREDIENTS: Cetylpyridinium Chloride 0.75 g/1 mL
INACTIVE INGREDIENTS: Water; Potassium Sorbate; Sodium Phosphate, Tribasic, Dodecahydrate; Anhydrous Citric Acid; Sodium Benzoate; Mint; Sucralose; Benzoic Acid

CloSYS Healthy Gums
Drug Facts

Active ingredient

Active ingredient | Purpose
Cetylpyridinium chloride 0.075 | Antigingivitis/Antiplaque

Uses

- Helps prevent and reduce plaque and gingivitis.
- Helps control plaque bacteria that contribute to the development of gingivitis, an early form of gum disease, and bleeding gums.

Warnings

Stop use and ask a dentist if

- gingivitis, bleeding, or redness persists for more than 2 weeks
- you have painful or swollen gums, pus from the gum line, loose teeth, or increasing spacing between the teeth. These may be signs or symptoms of periodontitis, a serious form of gum disease.

Keep out of reach of children under 6 years of age. If more than used for rinsing is accidentally swallowed, get medical help or contact a Poison Control Center right away.

Directions
Adults and children 12 years and over | Vigorously swish 20 milliliters of rinse between your teeth for 30 seconds and then spit out. Do not swallow rinse.
Children 6 years to under 12 years | Supervise use.
Children under 6 years | Do not use.

Other Information

- Do not use if safety seal is broken or missing.
- This rinse is not intended to replace brushing or flossing

INACTIVE INGREDIENT

Inactive ingredients water, potassium sorbate, trisodium phosphate, citric acid, sodium benzoate, mint flavor, sucralose, benzoic acid

Questions or comments?

call 1-800-643-3337

PACKAGE LABEL.PRINCIPAL DISPLAY PANEL

Non-Burning, Non-Irritating Formula
A CLEANER MOUTH
A HEALTHIER YOU®
ClōSYS®
Antigingivitis/Antiplaque Mouth Rinse
HEALTHY
GUMS
SENSITIVE
MOUTH RINSE
KILLS GERMS
THAT CAUSE GINGIVITIS, PLAQUE
& BAD BREATH
Helps Reverse Early Signs
of Gum Disease
Freshens Breath
Non Burning, Alcohol Free
Gentle Mint
32 fl oz (946 mL)

Our Story
Founder of CloSYS® & Periodontist Dr. Perry Ratcliff
had a bold belief that there had to be a better/gentler
way to help with oral care. Dr. Ratcliff didn’t agree
with the common myth ‘If it hurts, it must be good
for you.’
CloSYS® took a different approach―keep it gentle,
yet effective, and people will use it long enough
to make a difference in their oral health. After
discovering that his first patented formula was not
only extremely gentle but incredibly effective, he
gathered a small group of dental professionals and
business leaders to start their journey toward what
is today Founder of CloSYS® Oral Care.

What Makes CloSYS®
Products Different?
Simply put, CloSYS® is the Gentlest, Oral Care. Ever.®
All CloSYS® formulas are highly effective and
extremely gentle so they are not harsh or irritating to
sensitive mouths. And because it’s so gentle, it
means you can swish it in your mouth longer without
having to spit it out early and risk not getting the full
benefit of the rinse.
CloSYS® products are free of alcohol, sulfates,
triclosan, and other harsh ingredients that can
burn or irritate sensitive mouths.

How Does CloSYS®
Healthy Gums Work?
CloSYS® Healthy Gums Oral Rinse kills germs that
cause gingivitis, plaque and bad breath and helps
reverse early signs of gum disease (redness,
bleeding and inflammation).
Its gentle formula protects against plaque formation
that oftens leads to gingivitis, while the gentle mint
flavor freshens breath. And, the formula doesn’t
contain alcohol, sulfates, triclosan, and other
ingredients that can burn or irritate the mouth or
gums so you can rinse longer and get great results!
HEALTHY Mouth= HEALTHY Body
Gentlest.
Oral Care.
Ever.®

Distributed by:
Rowpar Pharmaceuticals, Inc.
Bridgewater, NJ 08807
1(800) 643-3337 closys.com

This bottle is recyclable. Please
support recycling in your community.

55002-44

A CLEANER MOUTH
A HEALTHIER YOU®
ClōSYS
Antigingivitis/Antiplaque Mouth Rinse
HEALTHY
GUMS
SENSITIVE
MOUTH RINSE
KILLS GERMS
THAT CAUSE GINGIVITIS, PLAQUE
& BAD BREATH
Helps Reverse Early Signs
of Gum Disease
Freshens Breath
Non Burning, Alcohol Free
Gentle Mint
32 fl oz (946 mL)
52532-85
Distributed by: Rowpar Pharmaceuticals, Inc.
Bridgewater, NJ 08807
1(800) 643-3337 closys.com
This bottle is recyclable. Please
support recycling in your community.
52532-86